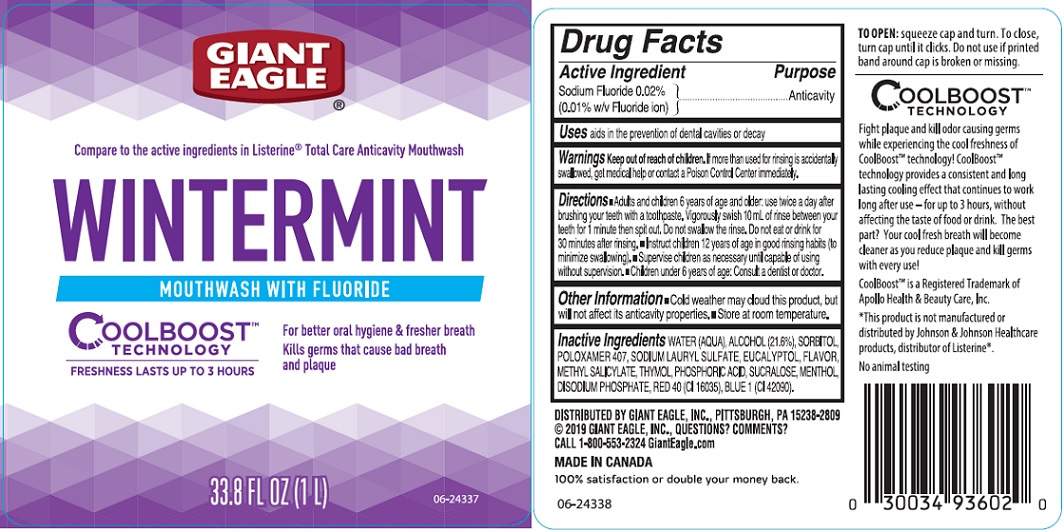 DRUG LABEL: Giant Eagle Wintermint With Fluoride
NDC: 63148-021 | Form: MOUTHWASH
Manufacturer: Apollo Health and Beauty Care Inc.
Category: otc | Type: HUMAN OTC DRUG LABEL
Date: 20191022

ACTIVE INGREDIENTS: SODIUM FLUORIDE 0.2 mg/1 mL
INACTIVE INGREDIENTS: WATER; ALCOHOL; SORBITOL; POLOXAMER 407; SODIUM LAURYL SULFATE; EUCALYPTOL; METHYL SALICYLATE; THYMOL; PHOSPHORIC ACID; SUCRALOSE; MENTHOL; SODIUM PHOSPHATE DIBASIC DIHYDRATE; FD&C RED NO. 40; FD&C BLUE NO. 1

Drug Facts

Active ingredient

Sodium Fluoride 0.02% (0.01% w/v Fluoride ion)

Purpose

Anticavity

Uses

aids in the prevention of dental cavities or decay

Warnings

Keep out of reach of children.

If more than used for rinsing is accidentally swallowed, get medical help or contact a Poison Control Center immediately.

Directions

- Adults and children 6 years of age and older: use twice a day after brushing your teeth with a toothpaste. Vigorously swish 10 mL of rinse between your teeth for 1 minute then spit out. Do not swallow the rinse. Do not eat or dring for 30 mins after rinsing.
- Instruct children 12 years of age in good rinsing habits (to minimize swallowing).
- Supervise children as necessary until capable of using without supervision.
- Children under 6 years of age: Consult a dentist or doctor.

Other information

- Cold weather may cloud this product, but will not affect its anticavity properties.
- Store at room temperature.

Inactive ingredients

Water (Aqua), Alcohol (21.6%), Sorbitol, Poloxamer 407, Sodium Lauryl Sulfate, Eucalyptol, Flavor, Methyl Salicylate, Thymol, Phosphoric Acid, Sucralose, Menthol, Disodium Phosphate, Red 40 (CI 16035), Blue 1 (CI 42090).